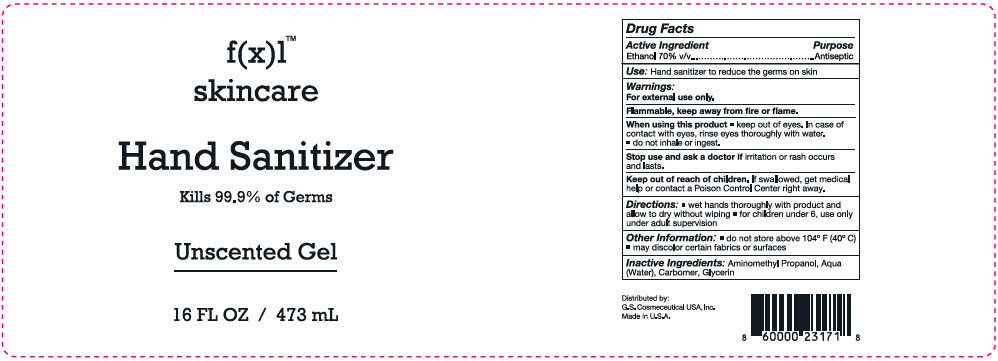 DRUG LABEL: f(x)l Skin Care Hand Sanitizer
NDC: 65113-1001 | Form: GEL
Manufacturer: G.S. COSMECEUTICAL USA, INC.
Category: otc | Type: HUMAN OTC DRUG LABEL
Date: 20220106

ACTIVE INGREDIENTS: Alcohol 70 mL/100 mL
INACTIVE INGREDIENTS: Water; Glycerin; Carbomer Interpolymer Type A (Allyl Sucrose Crosslinked); Semuloparin

f(x)l™ Skin Care Hand Sanitizer

Drug Facts

Active Ingredient

Ethanol 70% v/v

Purpose

Antiseptic

Use

Hand sanitizer to reduce the germs on skin

Warnings

For external use only.

Flammable, keep away from fire or flame.

When using this product

- keep out of eyes. In case of contact with eyes, rinse eyes thoroughly with water.
- do not inhale or ingest.

Stop use and ask a doctor if irritation or rash occurs and lasts.

Keep out of reach of children. If swallowed, get medical help or contact a Poison Control Center right away.

Directions

- wet hands thoroughly with product and allow to dry without wiping
- for children under 6, use only under adult supervision

Other Information

- do not store above 104° F (40° C)
- may discolor certain fabrics or surfaces

Inactive Ingredients

Aminomethyl Propanol, Aqua (Water), Carbomer, Glycerin

Distributed by:
G.S. Cosmeceutical USA, Inc.

PRINCIPAL DISPLAY PANEL - 473 mL Bottle Label

f(x)l™
skincare

Hand Sanitizer

Kills 99.9% of Germs

Unscented Gel

16 FL OZ / 473 mL